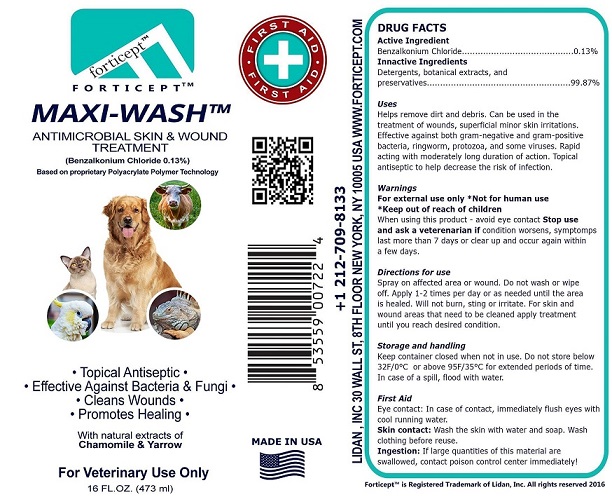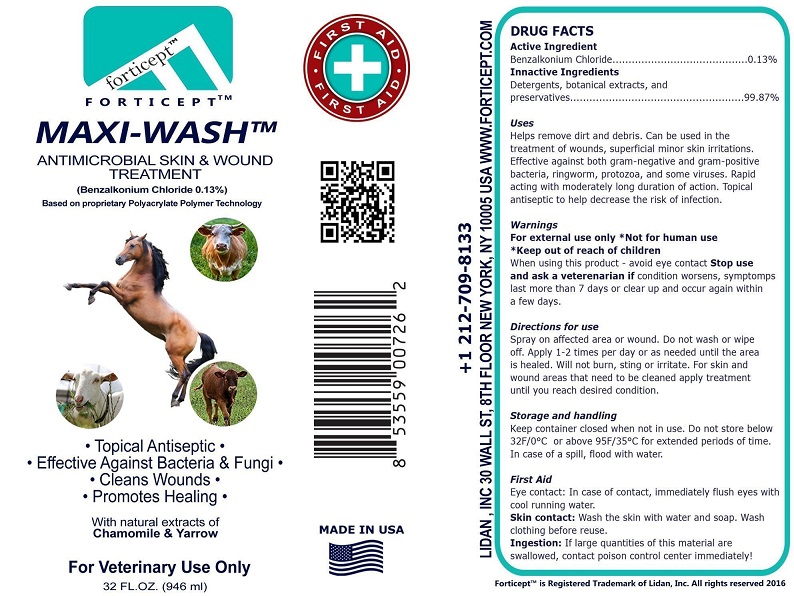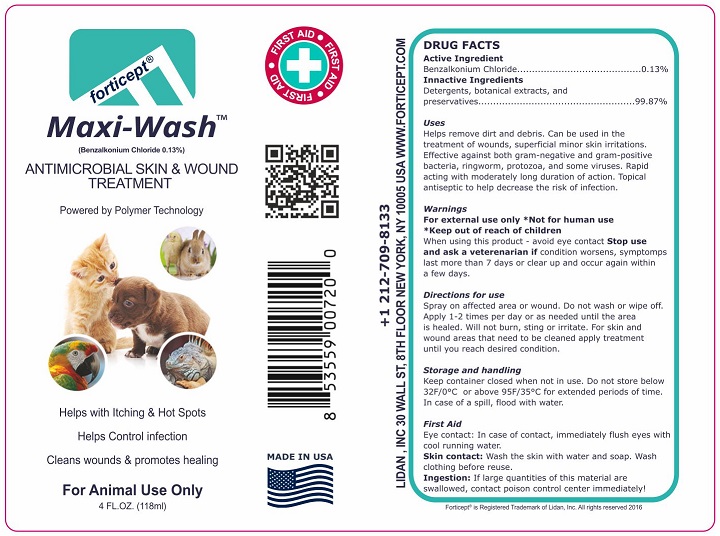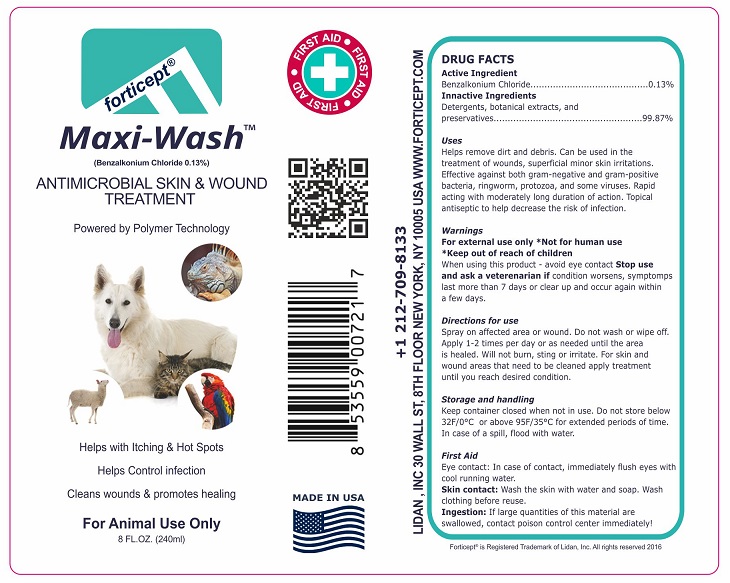 DRUG LABEL: Forticept Maxi Wash
NDC: 72127-0704 | Form: LIQUID
Manufacturer: Lidan, Inc.
Category: animal | Type: OTC ANIMAL DRUG LABEL
Date: 20240927

ACTIVE INGREDIENTS: benzalkonium chloride 1.3 g/1000 g

Active Ingredient

Benzakonium Chloride............0.13%

Inactive ingredients:

Detergents, botanical extracts, and preservatives……………………………………………..……….99.87%

Uses

Helps remove dirt and debris. Can be used in the treatment of wounds, superficial minor skin irritations. Effective against both gram-negative and gram-positive bacteria, ringworm, protozoa and some viruses. Rapid acting with a moderately long duration of action. Topical antiseptic to help decrease the risk of infection.

Warnings

For external use only * Not for human use * Keep out of reach of children

When using this product- avoid eye contact.

Stop use and ask a veterinarian if condition worsens, symptoms last more than 7 days or clear up and occur again within a few days.

Directions for use:

Spray on affected area or wound. Do not wash or wipe off. Apply 1-2 times per day or as needed until the area is healed. Will not burn, sting or irritate. For skin and wound areas that need to be cleaned apply treatment until you reach desired condition.

Storage and handling:

Keep container closed when not in use. Do not store below 32°F/0°C or above 95°F/35°C for extended periods of time. In case of spill, flood with water.

FIRST AID

Eye contact: In case of contact, immediately flush eyes with cool running water.

Skin contact: Wash the skin with water and soap. Wash clothing before reuse.

Ingestion: If large quantities of this material are swallowed, contact poison control center immediately!